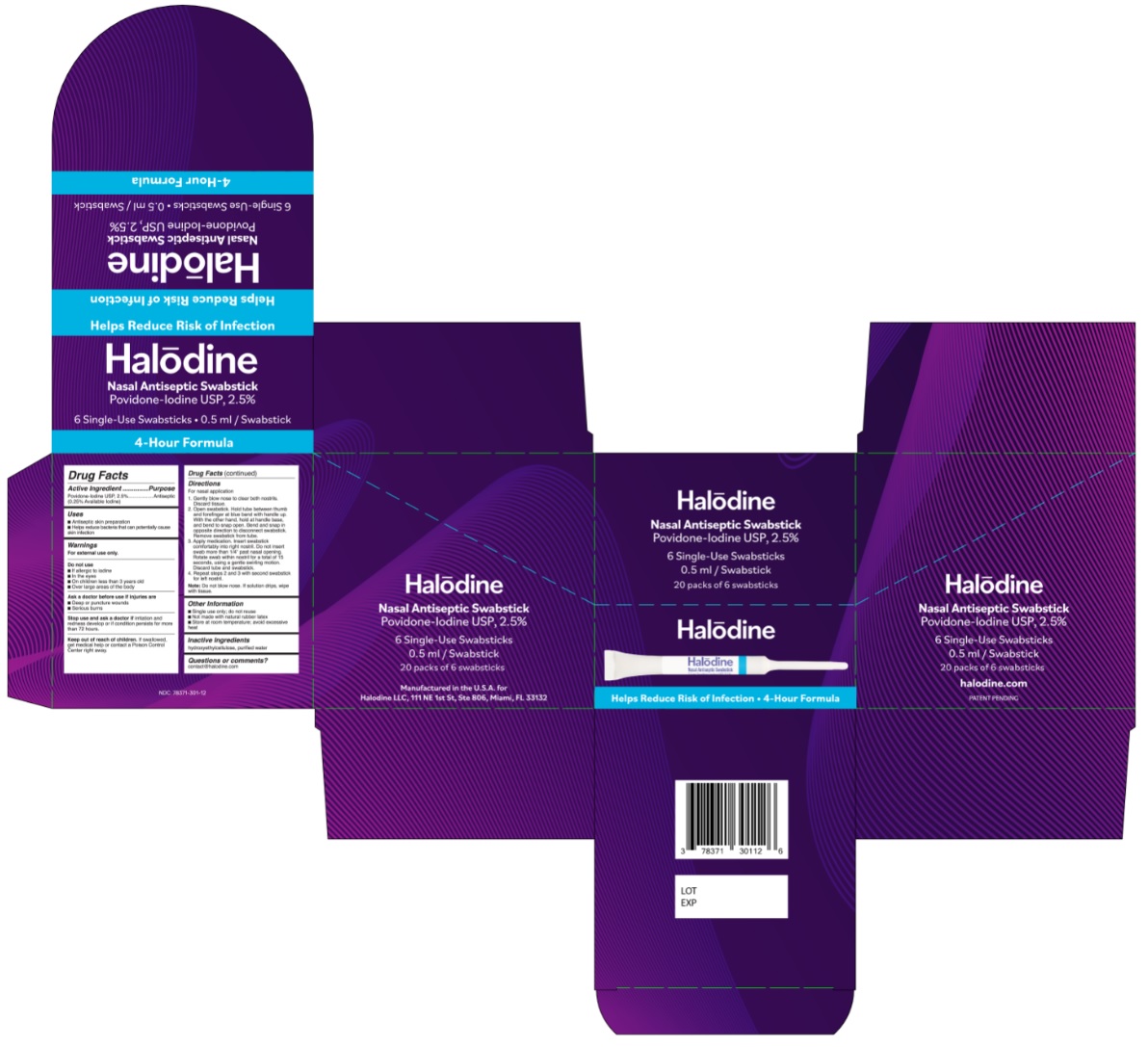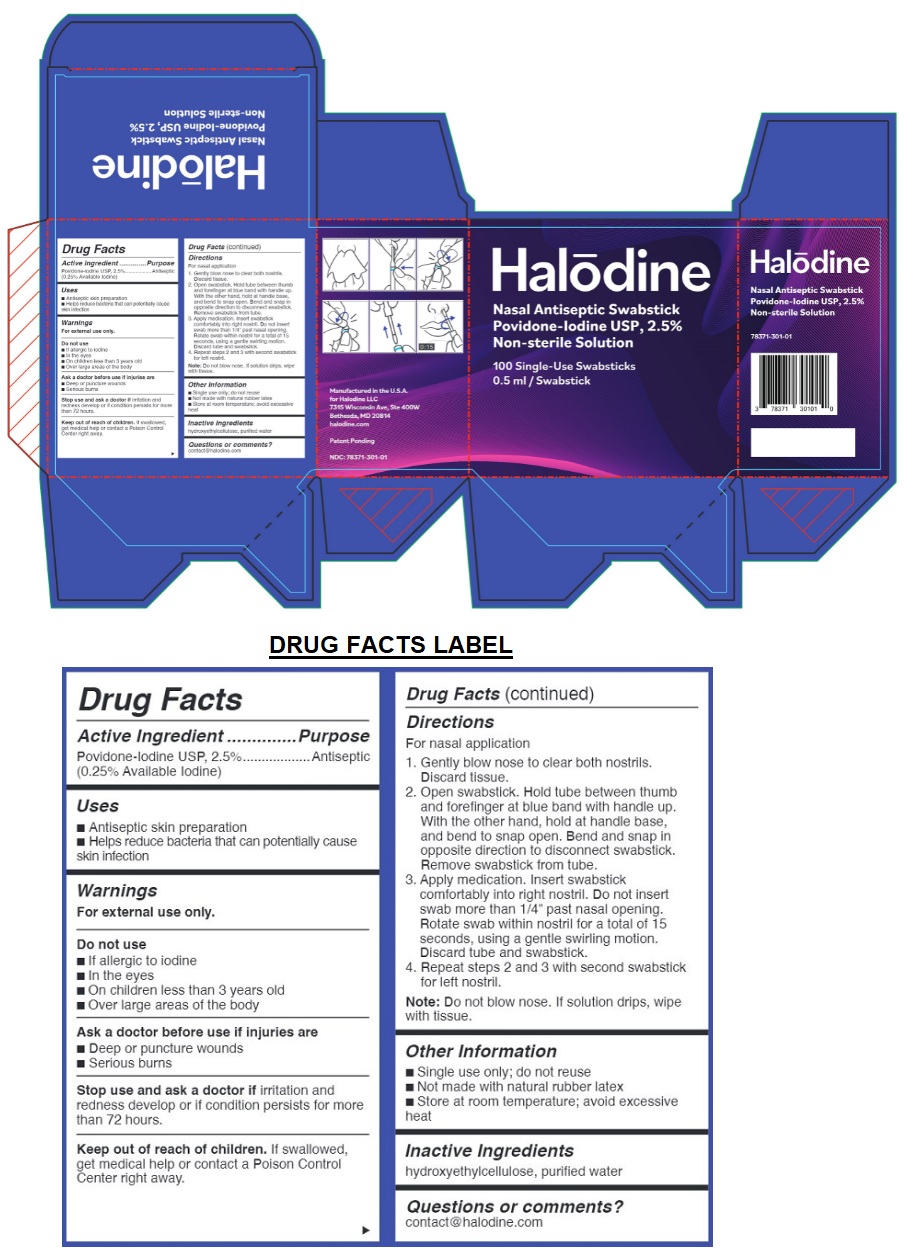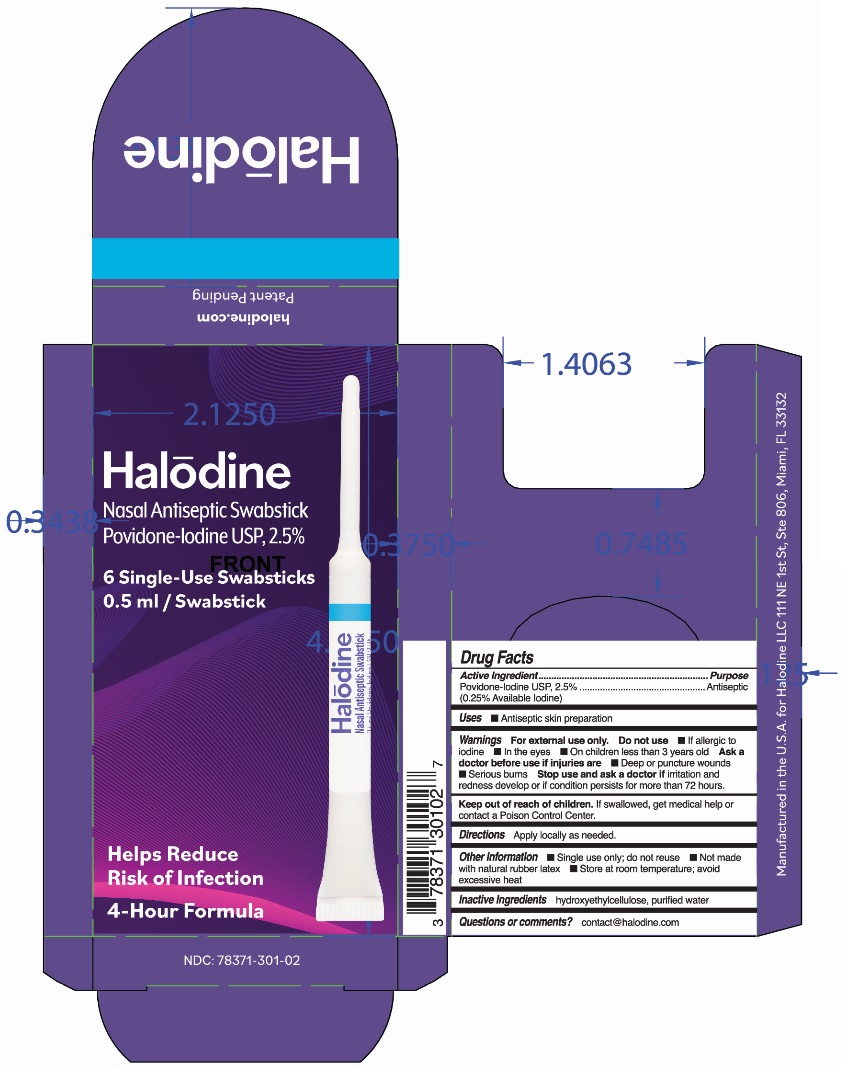 DRUG LABEL: Halodine Nasal Antiseptic Swabstick
NDC: 78371-301 | Form: SOLUTION
Manufacturer: Halodine LLC
Category: otc | Type: HUMAN OTC DRUG LABEL
Date: 20201007

ACTIVE INGREDIENTS: POVIDONE-IODINE 2.5 mg/1 mL
INACTIVE INGREDIENTS: HYDROXYETHYL CELLULOSE, UNSPECIFIED; WATER

Halodine Nasal Antiseptic Swabstick

Drug Facts

Active Ingredient

Povidone-Iodine USP, 2.5%
(0.25% Available Iodine)

Purpose

Antiseptic

Uses

- Antiseptic skin preparation
- Helps reduce bacteria that can potentially cause skin infection

Warnings

For external use only.

Do not use

- If allergic to iodine
- In the eyes
- On children less than 3 years old
- Over large areas of the body

Ask a doctor before use if injuries are

- Deep or puncture wounds
- Serious burns

Stop use and ask a doctor if

irritation and redness develop or if condition persists for more than 72 hours.

Keep out of reach of children.

If swallowed, get medical help or contact a Poison Control Center right away.

Directions

For nasal application

1. Gently blow nose to clear both nostrils. Discard tissue.
2. Open swabstick. Hold tube between thumb and forefinger at blue band with handle up. With other hand, hold handle at base, and bend to snap open. Bend and snap in opposite direction to disconnect swabstick. Remove swabstick from tube.
3. Apply medication. Insert swabstick comfortably into right nostril. Do not insert swab more than 1/4” past nasal opening. Rotate swab within nostril for a total of 15 seconds, using a gentle swirling motion. Discard tube and swabstick.
4. Repeat steps 2 and 3 with second swabstick for left nostril.

Note: Do not blow nose. If solution drips, wipe with tissue.

Other Information

- Single use only; do not reuse
- Not made with natural rubber latex
- Store at room temperature; avoid excessive heat

Inactive Ingredients

hydroxyethylcellulose, purified water

Questions or comments?

contact@halodine.com